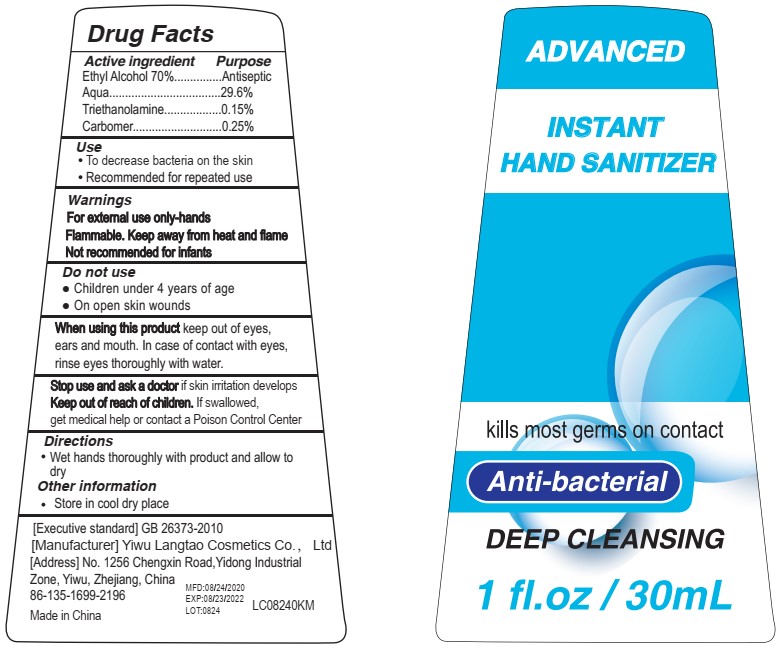 DRUG LABEL: INSTANT HAND SANITIZER
NDC: 77207-236 | Form: GEL
Manufacturer: Yiwu Langtao Cosmetics Co., Ltd
Category: otc | Type: HUMAN OTC DRUG LABEL
Date: 20200826

ACTIVE INGREDIENTS: ALCOHOL 70 mL/100 mL
INACTIVE INGREDIENTS: TROLAMINE 0.15 mL/100 mL; CARBOMER 980 0.25 mL/100 mL; WATER 29.6 mL/100 mL

Active Ingredient(s)

Ethyl Alcohol 70% v/v. Purpose: Antiseptic

Purpose

Antiseptic, Hand Sanitizer

Use

- To decrease bacteria on the skin
- Recommended for repeated use

Warnings

For external use only-hands. Flammable. Keep away from heat or flame. Not recommended for infants.

Do not use

- Children under 4 year of age
- on open skin wounds

When using this product keep out of eyes, ears, and mouth. In case of contact with eyes, rinse eyes thoroughly with water.
Stop use and ask a doctor if irritation or rash occurs. These may be signs of a serious condition.
Keep out of reach of children. If swallowed, get medical help or contact a Poison Control Center right away.

Stop use and ask a doctor if skin irritation develops.

Keep out of reach of children. If swallowed, get medical help or contact a Poison Control Center.

Directions

- Wet hands thoroughly with product and allow to dry
- Store in cool dry place

Inactive ingredients

carbomer,triethanolaminem water.

Package Label - Principal Display Panel

30 mL NDC: 77207-236-01